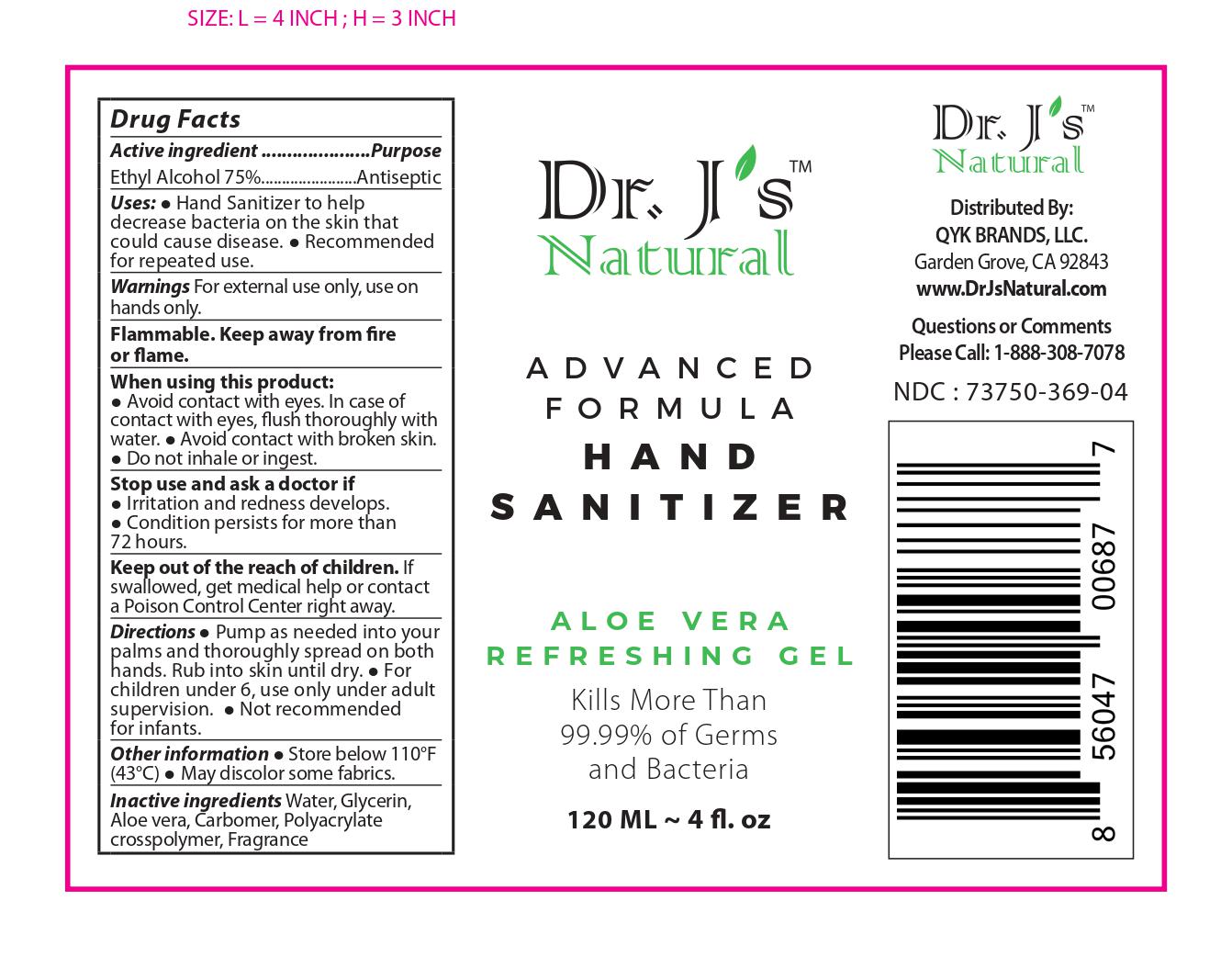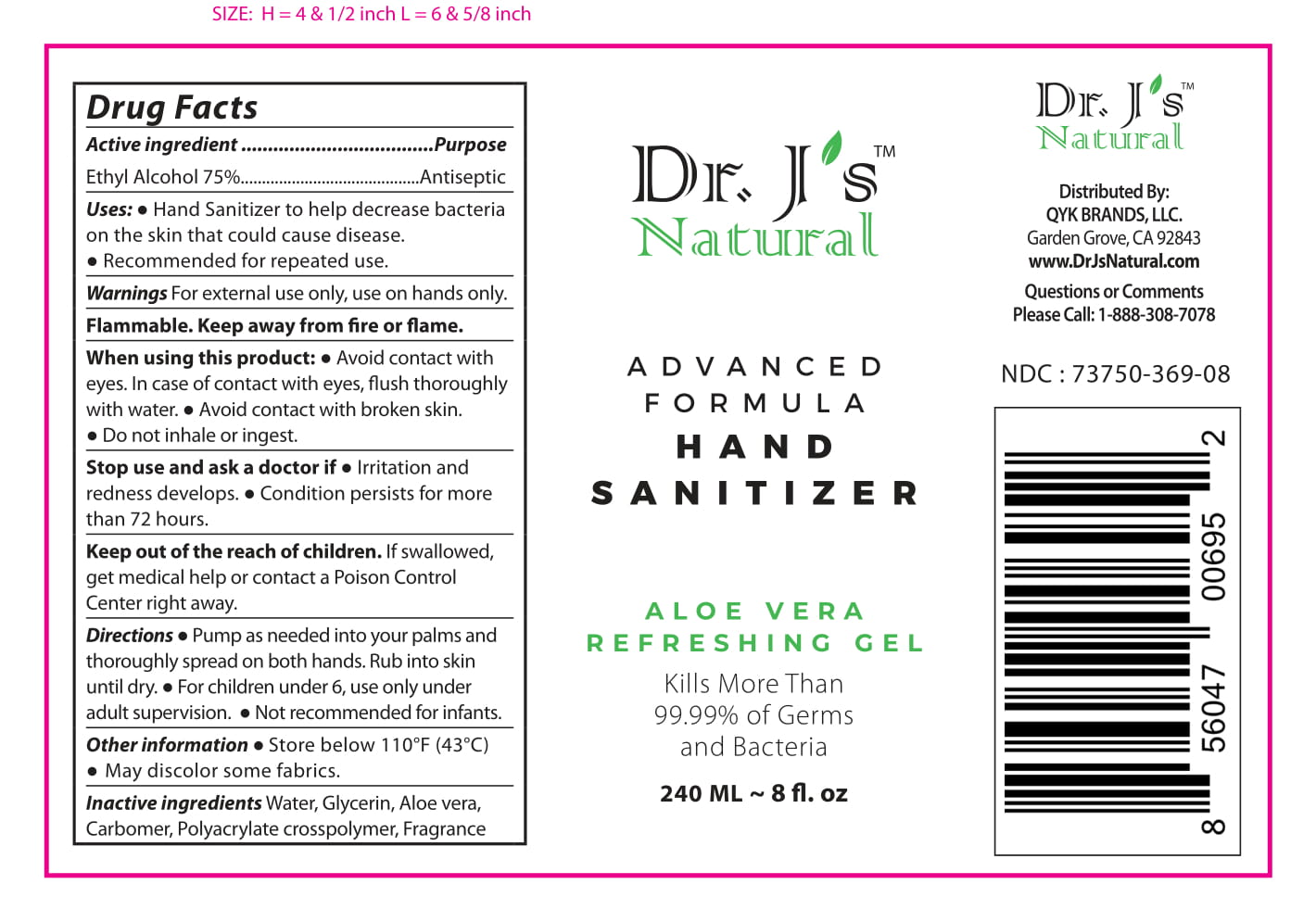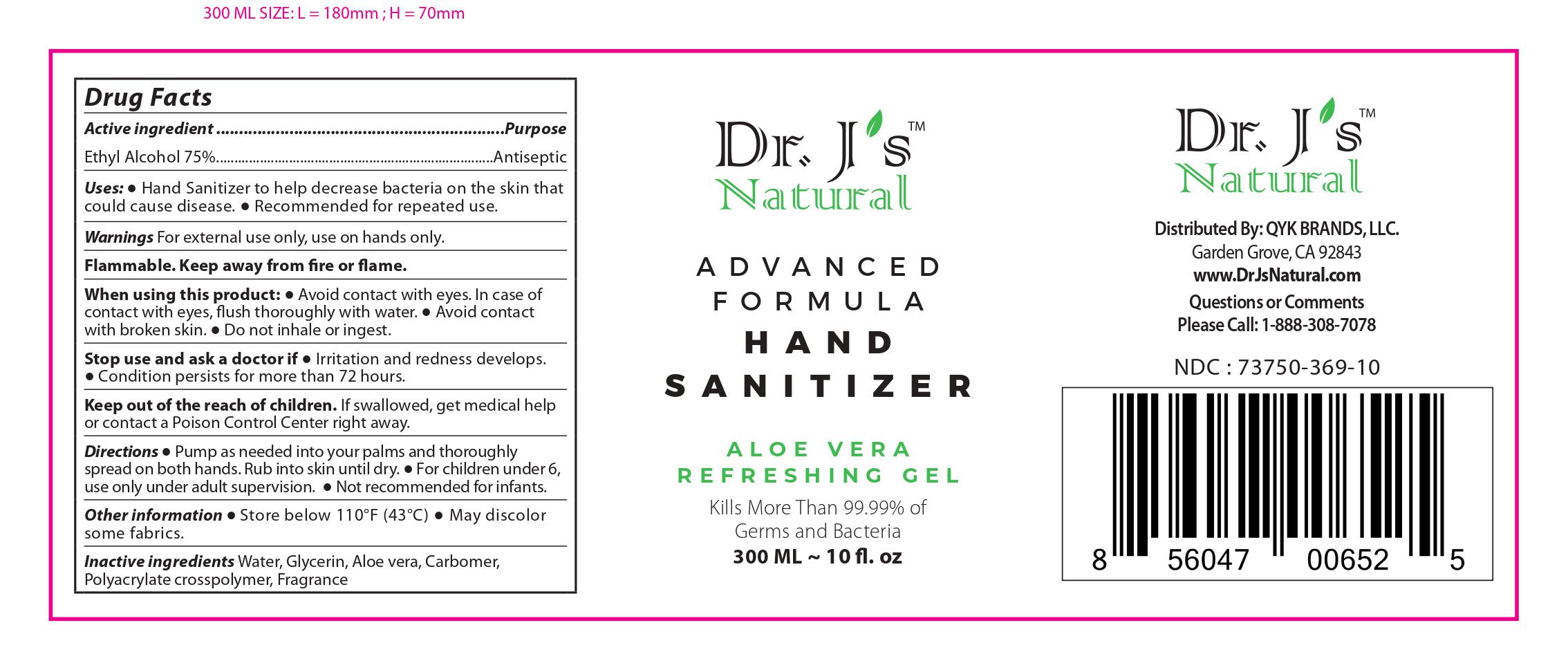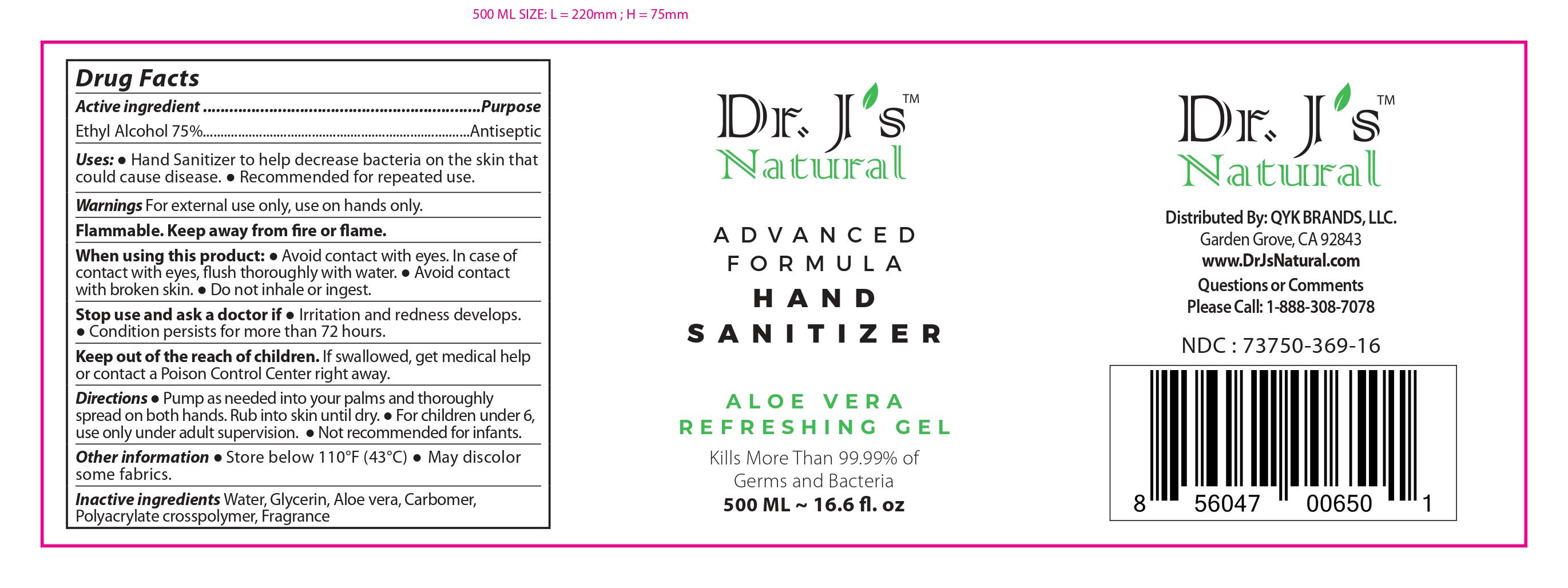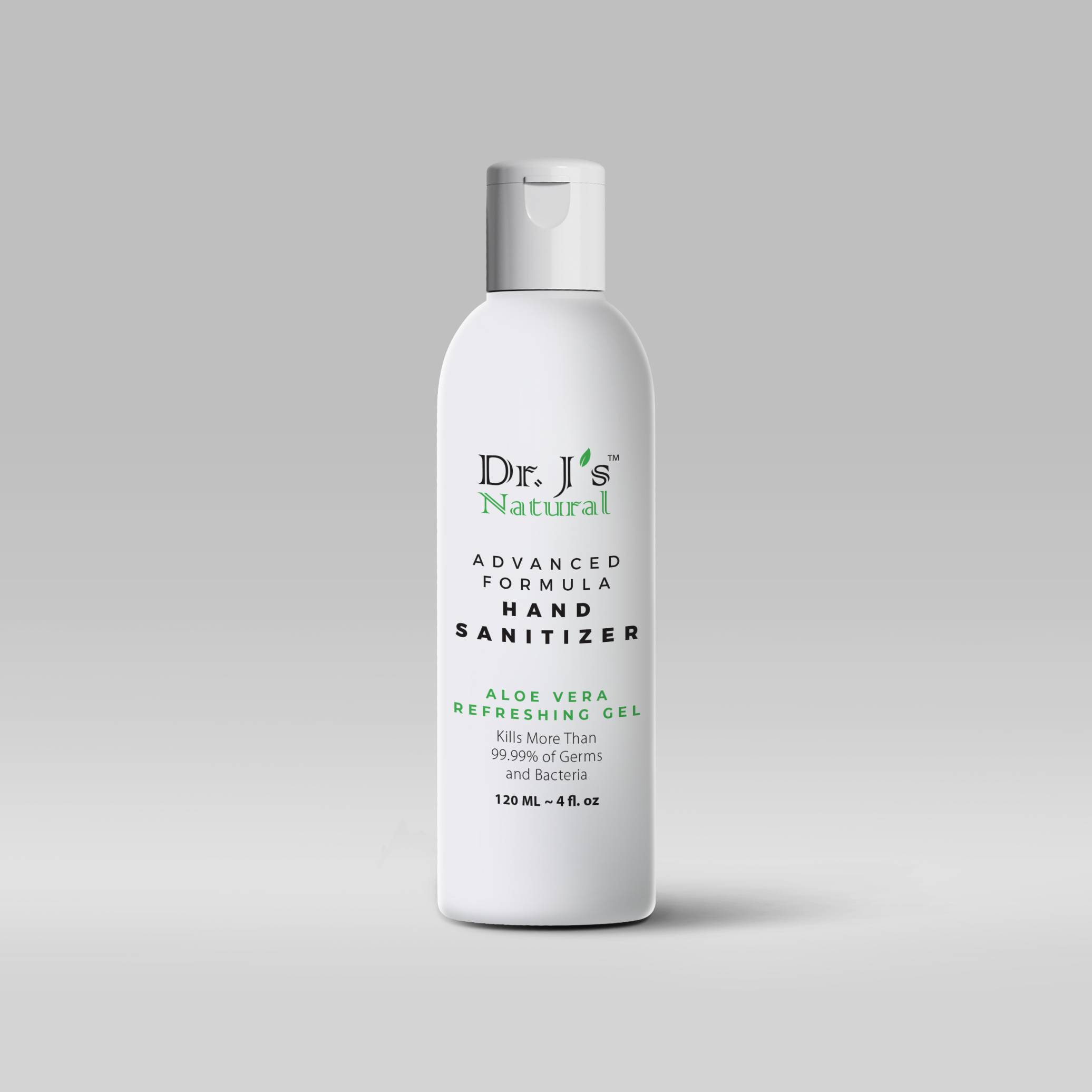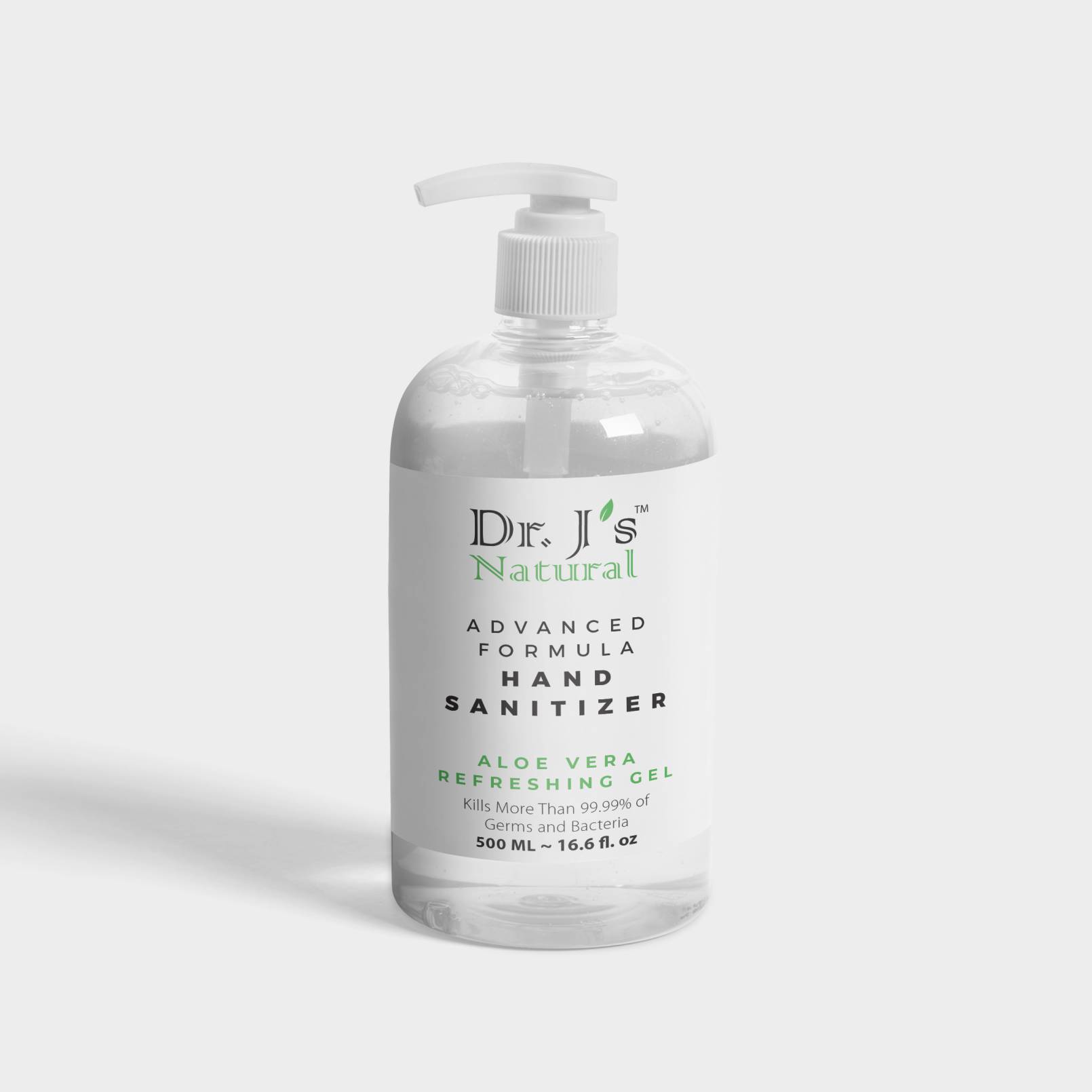 DRUG LABEL: Dr Js Natural Advanced Formula Hand Sanitizer
NDC: 73750-369 | Form: GEL
Manufacturer: QYK BRANDS LLC
Category: otc | Type: HUMAN OTC DRUG LABEL
Date: 20200415

ACTIVE INGREDIENTS: ALCOHOL 75 mL/100 mL
INACTIVE INGREDIENTS: WATER; ALOE VERA LEAF; CARBOMER HOMOPOLYMER, UNSPECIFIED TYPE; GLYCERIN; FRAGRANCE LAVENDER & CHIA F-153480

Active Ingredient

Ethyl Alcohol 75%

Purpose

Antimicrobial

Uses

● Hand Sanitizer to help decrease bacteria on the skin that could cause disease. ● Recommended for repeated use.

Warnings

Flammable. Keep away from fire or flame, For external use only.When using this product,do not use in or near the eyes.In case of contact,rinse eyes thoroughly with water.Stop use and ask doctor if irritation or rash appears and lasts,Keep out of reach for children if swallowed,get medical help of contact a Poison Control Center right away.

Do Not Use:

Stop use and ask a doctor if ● Irritation and redness develops. ● Condition persists for more than 72 hours.

When using this product:

● Avoid contact with eyes. In case of contact with eyes, flush thoroughly with water. ● Avoid contact with broken skin. ● Do not inhale or ingest.

Stop:

Stop use and ask a doctor if ● Irritation and redness develops. ● Condition persists for more than 72 hours.

Childeren Safety

Keep out of the reach of children. If swallowed, get medical help or contact a Poison Control Center right away.

Directions

Directions ● Pump as needed into your palms and thoroughly spread on both hands. Rub into skin until dry. ● For children under 6, use only under adult supervision. ● Not recommended for infants.

Other information

Store below 110°(43°C)

May discolor certain fabrics or surfaces

Inactive ingredients

Inactive ingredients Water, Glycerin, Aloe vera, Carbomer, Polyacrylate crosspolymer, Fragrance

PACKAGE LABEL

NDC